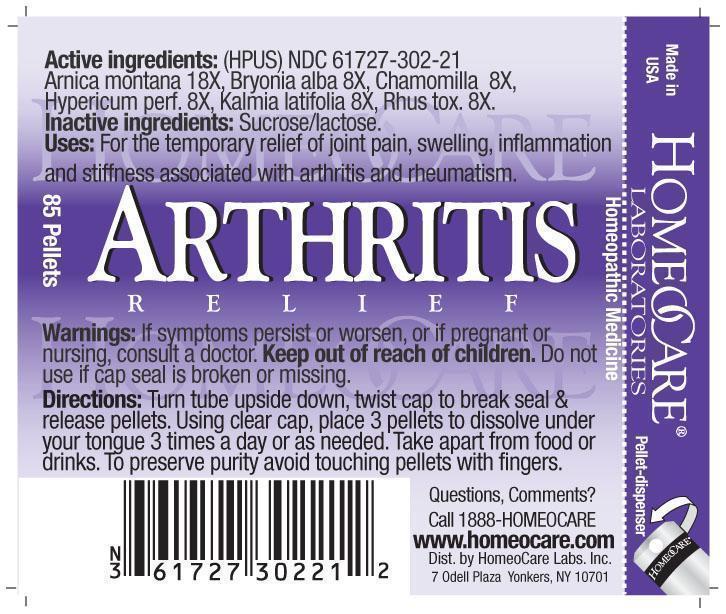 DRUG LABEL: Arthritis Relief
NDC: 61727-302 | Form: PELLET
Manufacturer: Homeocare Laboratories
Category: homeopathic | Type: HUMAN OTC DRUG LABEL
Date: 20260112

ACTIVE INGREDIENTS: ARNICA MONTANA 18 [hp_X]/4 g; BRYONIA ALBA ROOT 8 [hp_X]/4 g; MATRICARIA RECUTITA 8 [hp_X]/4 g; HYPERICUM PERFORATUM 8 [hp_X]/4 g; KALMIA LATIFOLIA LEAF 8 [hp_X]/4 g; TOXICODENDRON PUBESCENS LEAF 8 [hp_X]/4 g
INACTIVE INGREDIENTS: SUCROSE; LACTOSE

Arthritis Relief

Active Ingredients:

Arnica montana 18X, Bryonia alba 8X, Chamomilla 8X, Hypericum perf. 8X, Kalmia latifolia 8X, Rhus tox. 8X.

Inactive ingredients:

Sucrose/lactose.

Keep out of reach of children.

Purpose:

For the temporary relief of joint pain, swelling, inflammation and stiffness associated with arthritis and rheumatism.

Indications & Usage:

Turn tube upside down, twist cap to break seal & release pellets. Using clear cap, place 3 pellets to dissolve under your tongue 3 times a day or as needed. Take apart from food or drinks. To preserve purity avoid touching pellets with fingers.

Warnings:

If symptoms persist or worsen, or if pregnant or nursing, consult a doctor. Keep out of reach of children. Do not use if cap seal is broken or missing.

Dosage & Administration:

Turn tube upside down, twist cap to break seal & release pellets. Using clear cap, place 3 pellets to dissolve under your tongue 3 times a day or as needed. Take apart from food or drinks. To preserve purity avoid touching pellets with fingers.